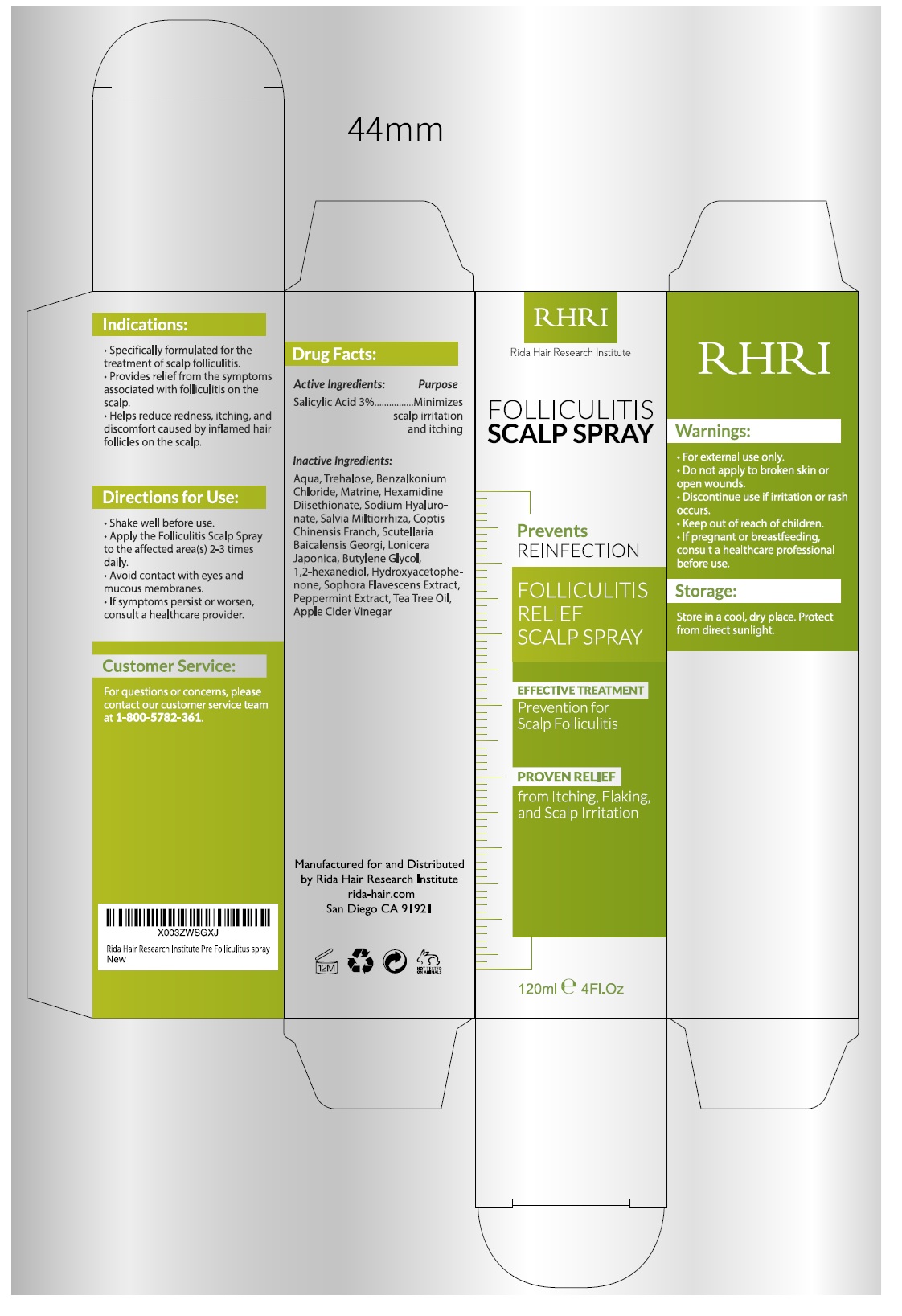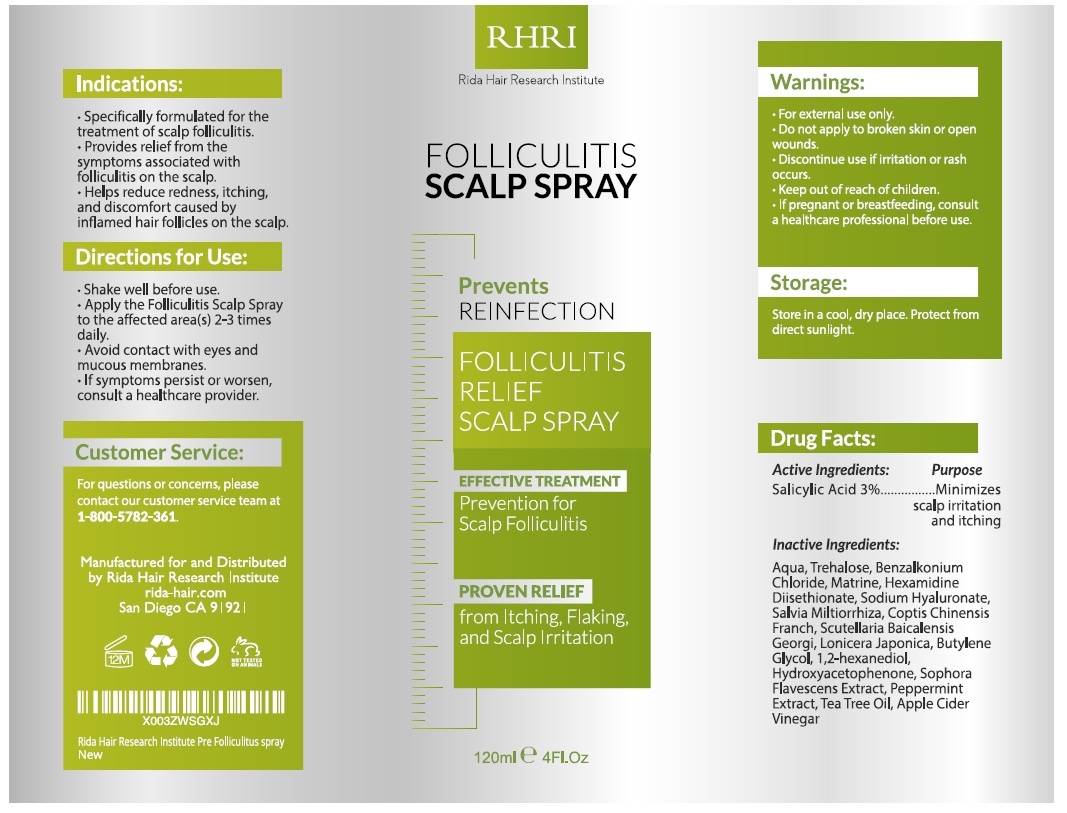 DRUG LABEL: Folliculitis Scalp
NDC: 83004-013 | Form: SPRAY
Manufacturer: Rida LLC
Category: otc | Type: HUMAN OTC DRUG LABEL
Date: 20250306

ACTIVE INGREDIENTS: SALICYLIC ACID 3 g/100 mL
INACTIVE INGREDIENTS: WATER; TREHALOSE; BENZALKONIUM CHLORIDE; MIRTAZAPINE; HEXAMIDINE; SODIUM HYALURONATE; GINKGO; 1,2-HEXANEDIOL; APPLE CIDER VINEGAR; BACILLUS SUBTILIS; COPTIS JAPONICA WHOLE; HYDROXYPROPYL GUAR HYDROXYPROPYLTRIMONIUM CHLORIDE; SALVIA MILTIORRHIZA ROOT; QUILLAJA SAPONARIA SAPONINS FRACTION C

Active Ingredient

Salicylic Acid 3%

Purpose

- Minimizes scalp irritation and itching

Uses

- Specifically formulated for the treatment of scalp folliculitis.
- Provides relief from symptoms associated with folliculitis on the scalp.
- Helps reduce redness, itching, and discomfort caused by inflamed hair follicles on the scalp.

Warnings

- For external use only.
- Do not apply to broken skin or open wounds.
- Discontinue use if irritation or rash occurs.
- Keep out of reach of children.
- If pregnant or breastfeeding, consult a healthcare professional before use.

Directions

- Shake well before use.
- Apply the Folliculitis Scalp Spray to the affected area 2–3 times daily.
- Avoid contact with eyes and mucous membranes.
- If symptoms persist or worsen, consult a healthcare provider.

Other Information

- Store in a cool, dry place. Protect from direct sunlight.

Inactive ingredients

Aqua (Water), Trehalose, Benzalkonium Chloride, Mirtazapine, Hexamidine, Sodium Hyaluronate, Salvia Miltiorrhiza Extract, Ginkgo Biloba Extract, Bacillus Subtilis Ferment, Coptis Chinensis Extract, 1,2-Hexanediol, Hydroxypropyl Guar, Saponins, Apple Cider Vinegar